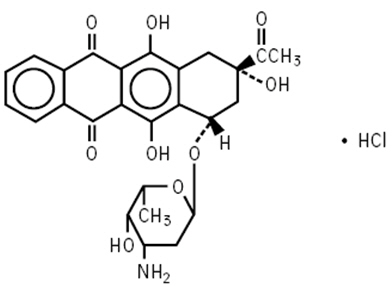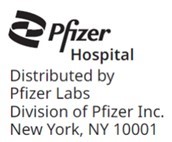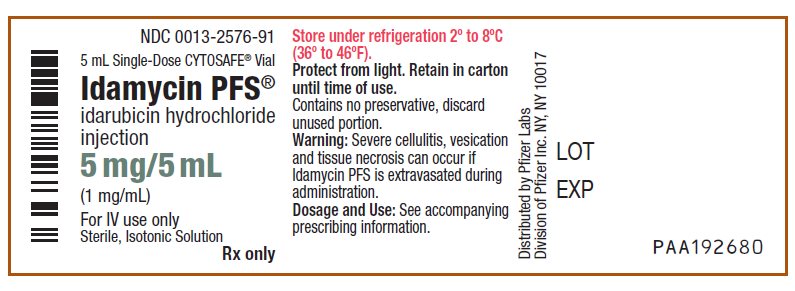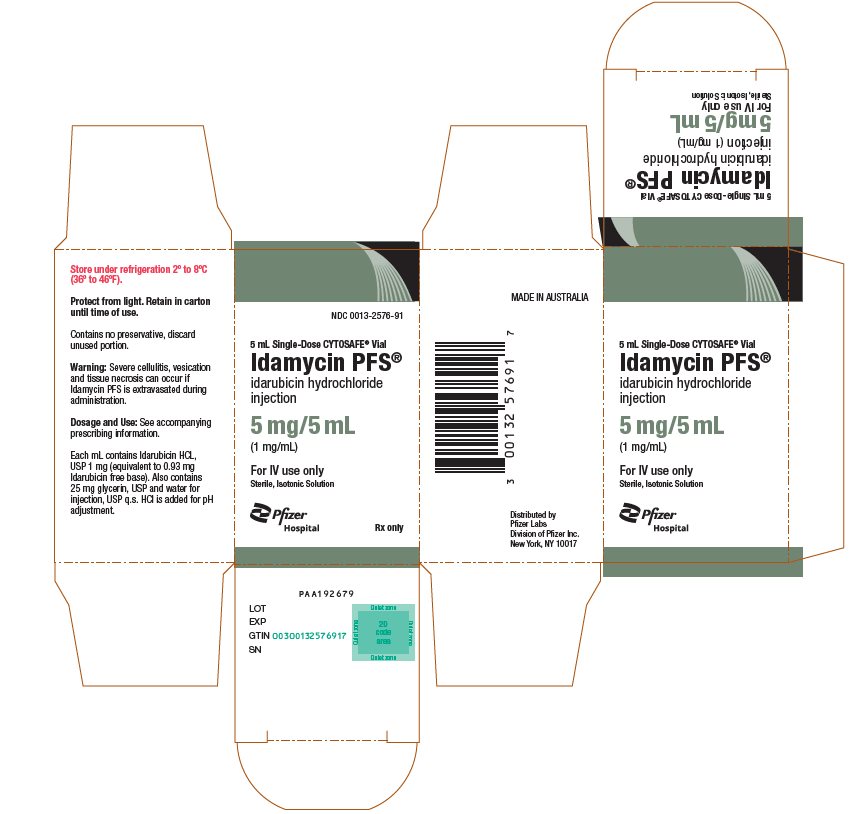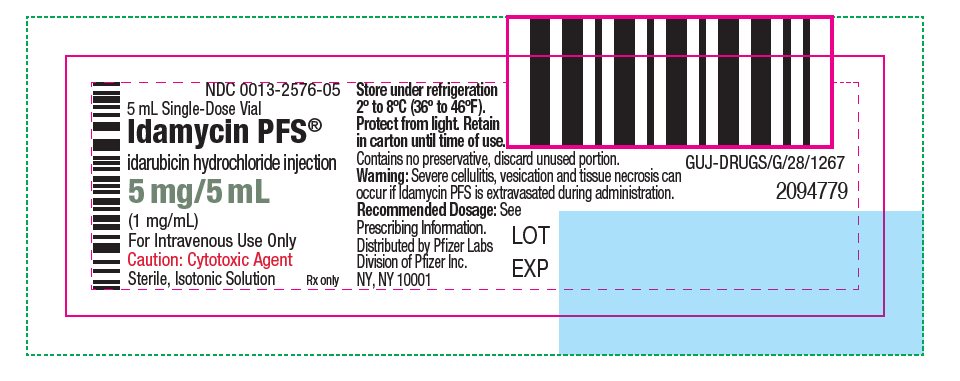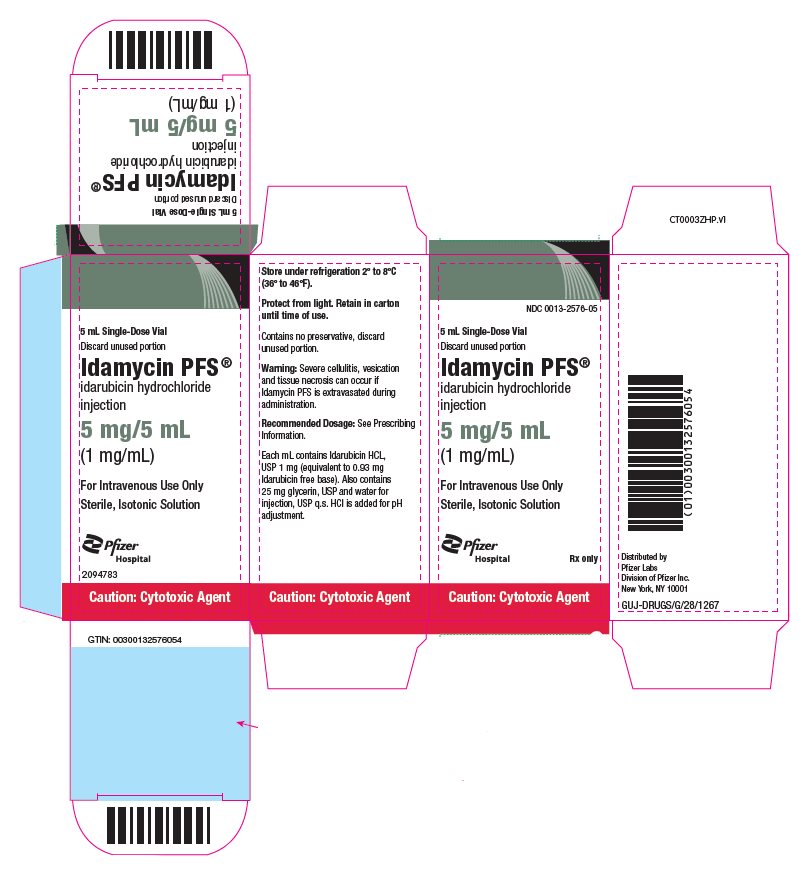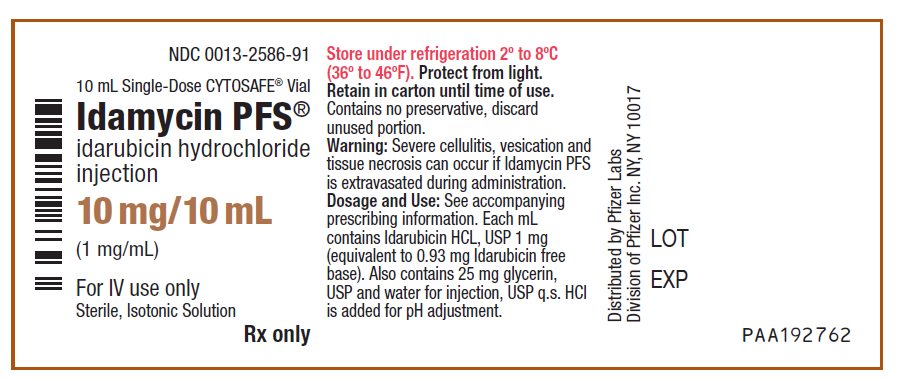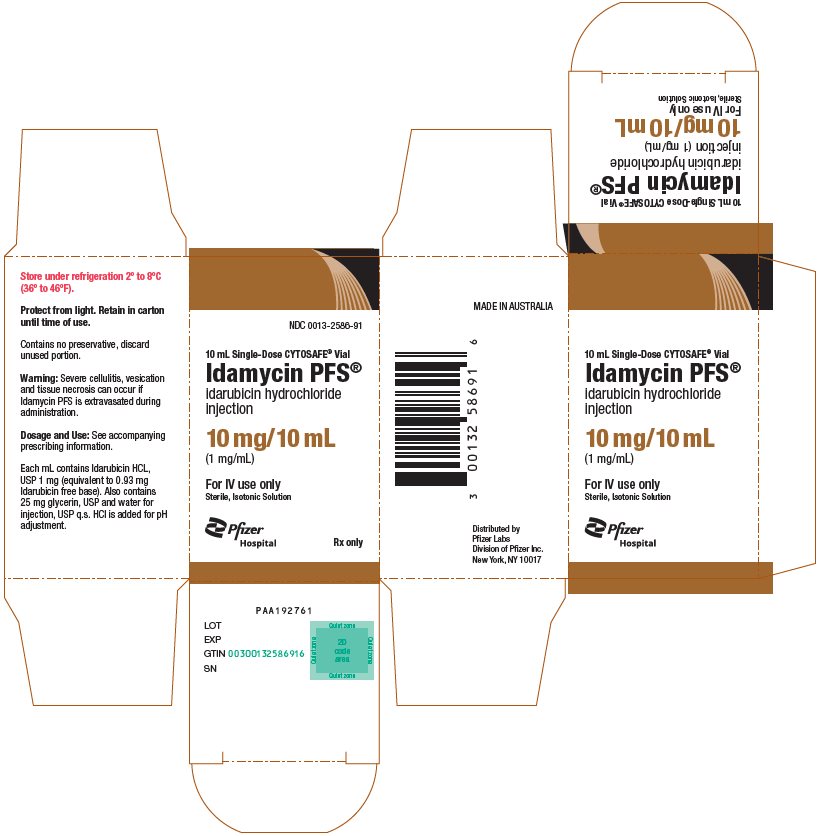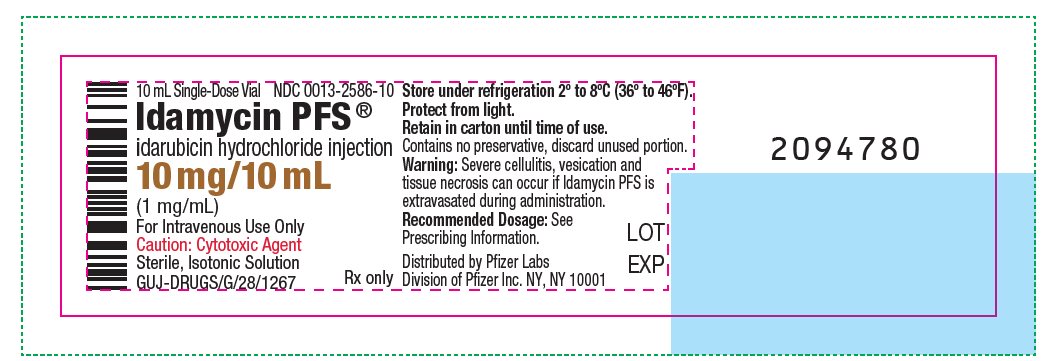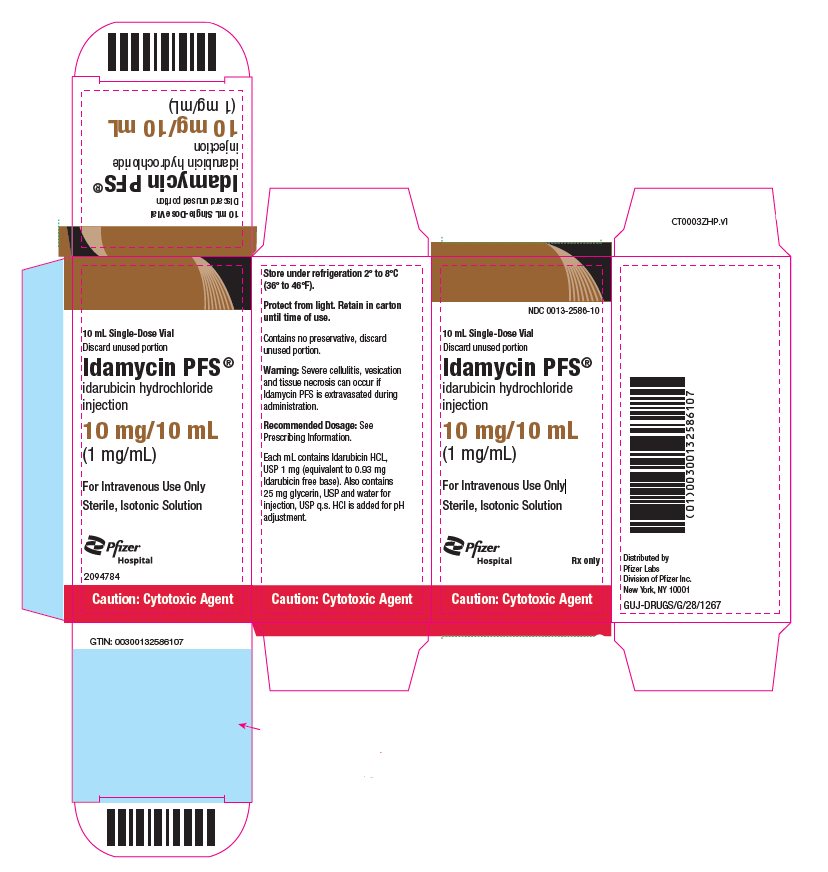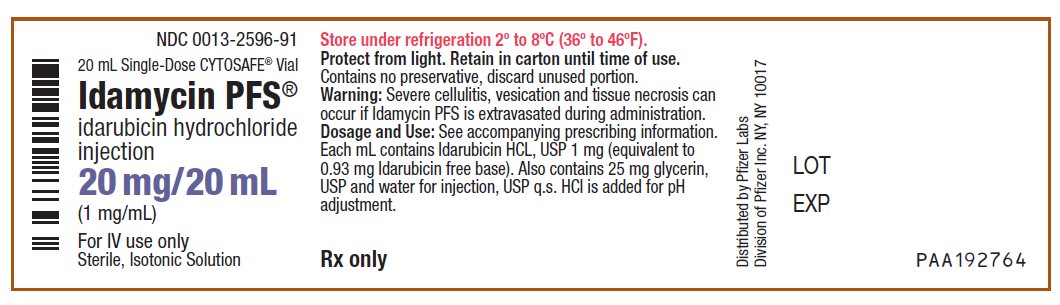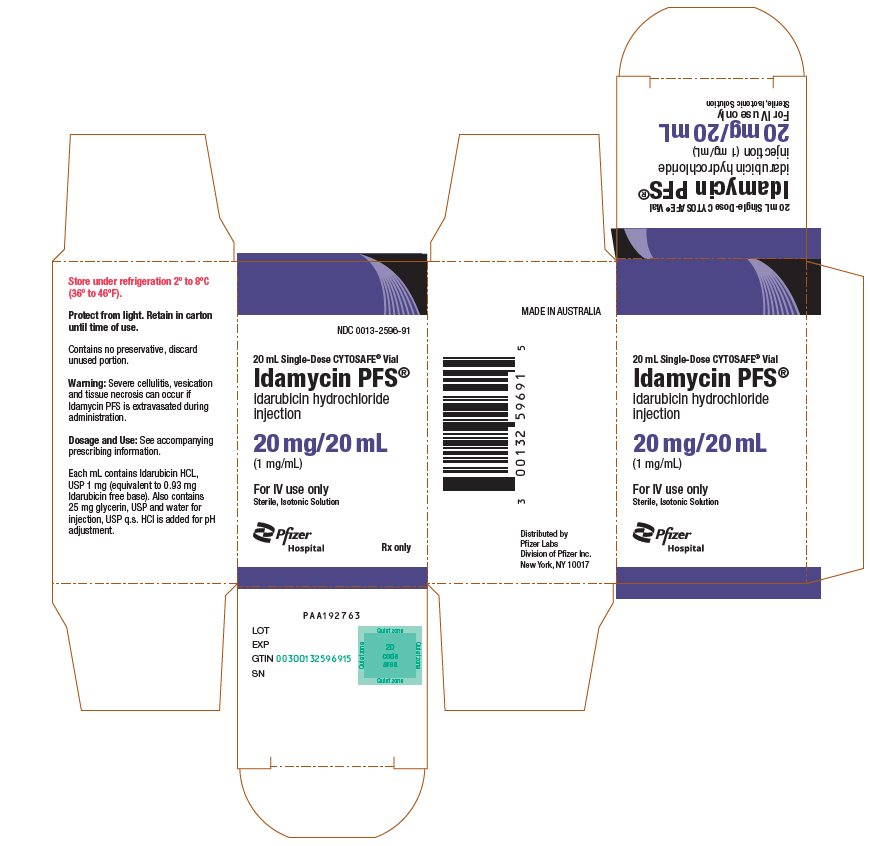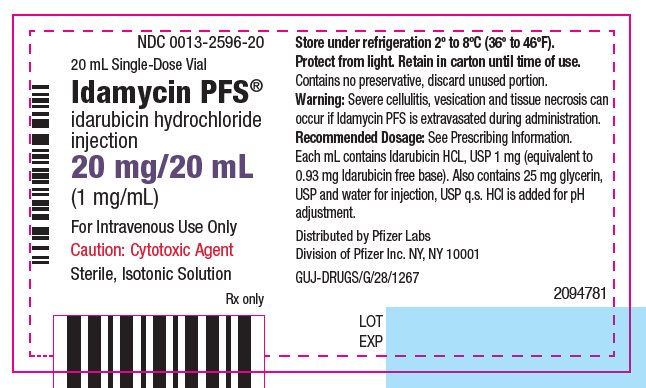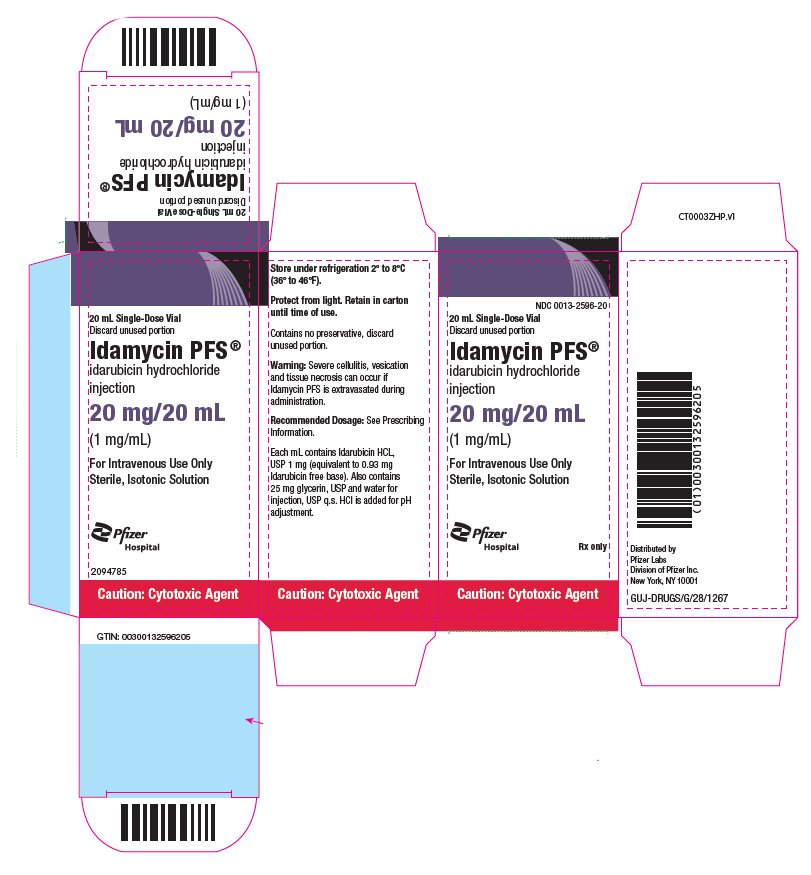 DRUG LABEL: Idamycin PFS
NDC: 0013-2576 | Form: SOLUTION
Manufacturer: Pfizer Laboratories Div Pfizer Inc
Category: prescription | Type: HUMAN PRESCRIPTION DRUG LABEL
Date: 20260219

ACTIVE INGREDIENTS: IDARUBICIN HYDROCHLORIDE 1 mg/1 mL
INACTIVE INGREDIENTS: GLYCERIN; WATER; HYDROCHLORIC ACID

HIGHLIGHTS OF PRESCRIBING INFORMATION

These highlights do not include all the information needed to use IDAMYCIN PFS safely and effectively. See full prescribing information for IDAMYCIN PFS.
IDAMYCIN PFS ® (idarubicin hydrochloride) injection, for intravenous use
Initial U.S. Approval: 1997

RECENT MAJOR CHANGES

Boxed Warning | 2/2026
Indications and Usage (1) | 2/2026
Dosage and Administration (2) | 2/2026
Warnings and Precautions (5) | 2/2026

WARNING: CARDIOMYOPATHY, SECONDARY MALIGNANCIES, and EXTRAVASATION AND TISSUE NECROSIS

See full prescribing information for complete boxed warning.

- Cardiomyopathy: Myocardial damage leading to congestive heart failure can occur with IDAMYCIN PFS. Assess left ventricular cardiac function prior to initiation of IDAMYCIN PFS and during and after treatment. (5.1)
- Secondary Malignancies: Secondary acute myelogenous leukemia (AML) and myelodysplastic syndrome (MDS) occur at a higher incidence in patients treated with anthracyclines, including IDAMYCIN PFS. (5.2)
- Extravasation of IDAMYCIN PFS during administration can result in local tissue injury and necrosis. Immediately discontinue the IDAMYCIN PFS infusion if extravasation occurs. (2.6, 5.3)

1 INDICATIONS AND USAGE

IDAMYCIN PFS is an anthracycline topoisomerase inhibitor indicated for the treatment of adult patients with acute myeloid leukemia (AML) as a component of a combination chemotherapy regimen. (1)

2 DOSAGE AND ADMINISTRATION

Induction Therapy

- 12 mg/m^2 intravenously over 10 to 15 minutes on days 1, 2, and 3 of induction in combination with cytarabine 100 mg/m^2 by continuous intravenous infusion daily for 7 days or cytarabine 25 mg/m^2 intravenous bolus followed by cytarabine 200 mg/m^2 continuous intravenous infusion daily for 5 days. (2.1)
- IDAMYCIN PFS can be given as part of a combination regimen with other chemotherapeutic drugs. (2.1)
- Renal Impairment: Assess renal function prior to therapy. Reduce dosage in renal impairment. (2.3, 8.6)
- Hepatic Impairment: Assess hepatic function prior to therapy. Avoid or reduce dosage in hepatic impairment. (2.4, 8.7)

See full prescribing information for preparation and administration instructions. (2.5, 2.6)

3 DOSAGE FORMS AND STRENGTHS

Injection: 5 mg/5 mL (1 mg/mL), 10 mg/10 mL (1 mg/mL), and 20 mg/20 mL (1 mg/mL) solution in a single-dose vial. (3)

4 CONTRAINDICATIONS

None. (4)

5 WARNINGS AND PRECAUTIONS

- Myelosuppression: Severe myelosuppression resulting in severe infection, septic shock, hemorrhage, or death may occur. Obtain complete blood counts prior to each treatment and closely monitor patients during treatment for possible clinical complications due to myelosuppression. (5.4)
- Tumor Lysis Syndrome: During treatment, monitor blood chemistries and manage promptly. Treat as clinically indicated. (5.5)
- Hypersensitivity: Monitor patients for hypersensitivity reactions and manage as clinically indicated. (5.6)
- Renal Impairment: Assess renal function prior to and during treatment. Reduce the dose in patients on dialysis or those with GFR <30 mL/min. (2.3, 5.7, 8.6)
- Hepatic Impairment: Obtain liver tests prior to and during therapy. Reduce dose in patients with serum bilirubin levels of 2.6 to 5 mg/dL. Avoid use in patients with serum bilirubin greater than 5 mg/dL. (2.4, 5.8, 8.7)
- Embryo-Fetal Toxicity: Can cause fetal harm. Advise patients of the potential risk to a fetus and to use effective contraception. (5.9, 8.1, 8.3)

6 ADVERSE REACTIONS

Most common adverse reactions (≥30%) are infection, nausea/vomiting, alopecia, abdominal pain/diarrhea, hemorrhage, mucositis, dermatologic, mental status changes, and pulmonary disorders. (6.1)

To report SUSPECTED ADVERSE REACTIONS, contact Pfizer at 1-800-438-1985 or FDA at 1-800-FDA-1088 or www.fda.gov/medwatch.

8 USE IN SPECIFIC POPULATIONS

- Lactation: Advise not to breastfeed. (8.2)
- Infertility: May impair fertility. (8.3)

FULL PRESCRIBING INFORMATION

WARNING: CARDIOMYOPATHY, SECONDARY MALIGNANCIES, and EXTRAVASATION AND TISSUE NECROSIS

- Cardiomyopathy: IDAMYCIN PFS can cause myocardial damage, including acute left ventricular failure, during or after termination of therapy. The risk of cardiomyopathy is increased in patients who have received prior anthracyclines or who have pre-existing cardiac disease. Assess left ventricular cardiac function prior to initiation of IDAMYCIN PFS and during and after treatment [see Warnings and Precautions (5.1)].
- Secondary Malignancies: Secondary acute myelogenous leukemia (AML) and myelodysplastic syndrome (MDS) occur at a higher incidence in patients treated with anthracyclines, including IDAMYCIN PFS [see Warnings and Precautions (5.2)].
- Extravasation and Tissue Necrosis: Extravasation of IDAMYCIN PFS during administration can result in local tissue injury and necrosis. Immediately terminate the infusion of IDAMYCIN PFS and institute the recommended management procedures [see Dosage and Administration (2.6) and Warnings and Precautions (5.3)].

1 INDICATIONS AND USAGE

IDAMYCIN PFS is indicated for the treatment of adult patients with acute myeloid leukemia (AML) as a component of a combination chemotherapy regimen.

2 DOSAGE AND ADMINISTRATION

2.1 Recommended Dosage

Administer IDAMYCIN PFS 12 mg/m^2 intravenously over 10 to 15 minutes on days 1, 2, and 3 of induction in combination with cytarabine. The cytarabine may be given as 100 mg/m^2 by continuous intravenous infusion daily for 7 days or as cytarabine 25 mg/m^2 intravenous bolus followed by cytarabine 200 mg/m^2 continuous intravenous infusion daily for 5 days.

If a response is not achieved with the first induction cycle, a second induction cycle may be administered. Other dosage regimens may be used for a second induction cycle.

Individualize the dose and dosing schedule of IDAMYCIN PFS based on the specific regimen administered, disease state, response to treatment, and patient risk factors.

2.2 Dosage Modifications for Adverse Reactions

Cardiomyopathy

Discontinue IDAMYCIN PFS in patients who develop signs or symptoms of cardiomyopathy [see Warnings and Precautions (5.1)].

Myelosuppression

If patients develop severe myelosuppression, reduce the dose of IDAMYCIN PFS by 25% or as clinically indicated in subsequent cycles [see Warnings and Precautions (5.4)].

Mucositis

If patients develop severe mucositis with IDAMYCIN PFS, reduce the dose by 25% in subsequent cycles. If a second cycle is planned, delay administration in patients who develop severe mucositis until this adverse reaction has resolved [see Adverse Reactions (6.1)].

2.3 Recommended IDAMYCIN PFS Dosage in Patients with Renal Impairment

In patients with renal impairment, reduce the dose of IDAMYCIN PFS as described in Table 1 [see Use in Specific Populations (8.6)].

Table 1: Recommended IDAMYCIN PFS Dosage for Patients with Renal Impairment

Renal Impairment/Estimated GFR | Dosage Modification
GFR greater than or equal to 30 mL/min | No adjustment needed
GFR less than 30 mL/min | Reduce the dose by 33%
Hemodialysis | Reduce the dose by 33%

2.4 Recommended IDAMYCIN PFS Dosage in Patients with Hepatic Impairment

In patients with hepatic impairment, reduce the dose of IDAMYCIN PFS as described in Table 2 [see Use in Specific Populations (8.7)].

Table 2: Recommended IDAMYCIN PFS Dosage for Patients with Hepatic Impairment

Serum Bilirubin | Dosage
Less than or equal to 2.6 mg/dL | No adjustment needed
Greater than 2.6 mg/dL and less than 5 mg/dL | Reduce the dose by 50%
Greater than 5 mg/dL | Avoid Use

2.5 Preparation

- IDAMYCIN PFS is a hazardous drug. Follow applicable special handling and disposal procedures.^1
- Do not mix IDAMYCIN PFS or administer as an infusion with other drugs or heparin.
- Avoid prolonged contact with any solution of an alkaline pH, as this will result in degradation of IDAMYCIN PFS.
- Parenteral drug products should be inspected visually for particulate matter and discoloration prior to administration, whenever solution and container permit.
- Withdraw the volume of IDAMYCIN PFS needed based on the required dose.
- Do not further dilute prior to administration (see section 2.6 Administration).
- Discard unused portion.

2.6 Administration

- IDAMYCIN PFS is for intravenous infusion only.
- Prior to administration, flush the intravenous catheter used for IDAMYCIN PFS administration to ensure patency and to minimize the risk of extravasation.
- Administer IDAMYCIN PFS over 10 to 15 minutes into the tubing of a freely running intravenous infusion of 0.9% Sodium Chloride Injection or 5% Dextrose Injection.
- Closely monitor the infusion site for extravasation or drug infiltration during administration. Manage cases of extravasation as per institutional guidelines.
- Immediately discontinue the infusion if extravasation occurs [see Warnings and Precautions (5.3)].

3 DOSAGE FORMS AND STRENGTHS

Injection: 5 mg/5 mL (1 mg/mL), 10 mg/10 mL (1 mg/mL), and 20 mg/20 mL (1 mg/mL) of idarubicin hydrochloride as a clear, orange-red, preservative-free aqueous solution in a single-dose vial.

4 CONTRAINDICATIONS

None.

5 WARNINGS AND PRECAUTIONS

5.1 Cardiomyopathy

IDAMYCIN PFS can cause myocardial damage, including left ventricular failure, or congestive heart failure (CHF). In pediatric patients, anthracycline-induced cardiomyopathy included impaired left ventricular systolic performance, reduced contractility, congestive heart failure, or death. Cardiomyopathy may develop during treatment with IDAMYCIN PFS or up to several years after completion of treatment. Cases of pericarditis and myocarditis have also been reported at a lower incidence and may not be dose related.

The risk of cardiomyopathy is generally proportional to the cumulative exposure to anthracycline drugs. Include prior doses of other anthracyclines or anthracenediones in calculations of total cumulative dosage for idarubicin hydrochloride. In adult patients, at cumulative doses exceeding 90 mg/m^2 of idarubicin hydrochloride, there is an increased incidence of drug-induced congestive heart failure. The tolerable limit may be lower in patients who received radiation therapy to the mediastinum. Concomitant use of cardiotoxic drugs may increase the risk of idarubicin-induced cardiac toxicity or may result in cardiotoxicity at a lower cumulative anthracycline dose.

Calculate the lifetime cumulative anthracycline exposure prior to each cycle of IDAMYCIN PFS. IDAMYCIN PFS use is not recommended in patients whose lifetime anthracycline exposure has reached the maximum cumulative limit.

Assess left ventricular cardiac function (e.g., MUGA or echocardiogram) prior to initiation of IDAMYCIN PFS. Perform serial cardiac monitoring, which may include electrocardiograms and/or determination of systolic ejection fraction, in all patients during treatment to detect acute changes and after treatment to detect delayed cardiotoxicity. Increase the frequency of assessments as the cumulative anthracycline dose increases or in patients with risk factors for cardiac toxicity. Consider long-term periodic evaluation of cardiac function in these patients.

Adults 65 years of age and older, or with pre-existing cardiac disease, may have an increased risk of anthracycline-induced cardiac toxicity, or may experience cardiotoxicity at a lower cumulative anthracycline dose.

Discontinue IDAMYCIN PFS in patients who develop signs or symptoms of cardiomyopathy.

5.2 Secondary Malignancies

The risk of developing secondary AML and myelodysplastic syndrome (MDS) is increased following treatment with IDAMYCIN PFS. AML and MDS have occurred in patients treated with anthracycline topoisomerase inhibitors when used in combination with other antineoplastic agents or radiation therapy. Monitor patients long-term for the development of secondary malignancies.

5.3 Severe Local Tissue Necrosis with Extravasation

Extravasation of IDAMYCIN PFS at the site of intravenous administration can cause severe local tissue injury including blistering, ulceration, thrombophlebitis, and necrosis requiring wide excision of the affected area and skin grafting.

Monitor patients during the IDAMYCIN PFS infusion for signs and symptoms of extravasation (including erythematous streaking, burning, or stinging sensations, thrombosis) or perivenous infiltration.

If extravasation occurs during administration, immediately discontinue the intravenous injection or continuous intravenous infusion of IDAMYCIN PFS and manage per institutional guidelines [see Dosage and Administrations (2.6)].

5.4 Severe Myelosuppression

Severe myelosuppression resulting in severe infection, septic shock, hemorrhage, or death may occur during treatment with IDAMYCIN PFS, and some patients may require blood product transfusions.

Obtain complete blood counts prior to each treatment and closely monitor patients during treatment for possible clinical complications due to myelosuppression. Delay next dose of IDAMYCIN PFS if severe myelosuppression has not improved. Consider dose reduction for patients with prolonged myelosuppression [see Dosage and Administrations (2.2)].

Discontinue IDAMYCIN PFS in patients who develop severe myelosuppression.

5.5 Tumor Lysis Syndrome

IDAMYCIN PFS may induce tumor lysis syndrome. Patients at risk of tumor lysis syndrome are those with rapidly growing tumors or high tumor burden prior to treatment.

During and after initial treatment, monitor blood chemistries and manage abnormalities promptly. Hydration, urine alkalinization, and prophylaxis with allopurinol to prevent hyperuricemia may minimize potential complications of tumor lysis syndrome.

5.6 Hypersensitivity

IDAMYCIN PFS can cause hypersensitivity reactions.

Clinical signs and symptoms of hypersensitivity may include, but are not limited to, rash and urticaria [see Adverse Reactions (6.1)]. Monitor patients for signs and symptoms of hypersensitivity during treatment with IDAMYCIN PFS and manage as clinically indicated.

5.7 Use in Patients with Renal Impairment

Renal impairment may result in increased risk of toxicity in patients treated with IDAMYCIN PFS [see Use in Specific Populations (8.6)].

Assess renal function prior to and during treatment with IDAMYCIN PFS.

Reduce the dose of IDAMYCIN PFS in patients on dialysis or those with GFR <30 mL/min [see Dosage and Administration (2.3)].

5.8 Use in Patients with Hepatic Impairment

Hepatic impairment may result in increased risk of toxicity in patients treated with IDAMYCIN PFS [see Use in Specific Populations (8.7)].

Obtain liver tests including ALT, AST, alkaline phosphatase, and bilirubin prior to and during therapy.

Reduce the dose of IDAMYCIN PFS in patients with serum bilirubin levels of 2.6 to 5 mg/dL. Avoid use of IDAMYCIN PFS in patients with serum bilirubin greater than 5 mg/dL [see Dosage and Administration (2.4)].

5.9 Embryo-Fetal Toxicity

Based on findings from animal reproductive studies and its mechanism of action [see Clinical Pharmacology (12.1)], IDAMYCIN PFS can cause fetal harm when administered to pregnant women. Idarubicin hydrochloride was embryotoxic and teratogenic in rats at doses of 1.2 mg/m^2/day or 0.1 times the human dose, which was not maternally toxic. Idarubicin hydrochloride was embryotoxic but not teratogenic in rabbits at doses of 2.4 mg/m^2/day or 0.2 times the human dose, which was maternally toxic. Advise women of the potential risk to the fetus.

Advise females of reproductive potential to use effective contraception during treatment with IDAMYCIN PFS and for 6.5 months after the last dose. Advise males with female partners of reproductive potential to use effective contraception for 3.5 months after the last dose [see Use in Specific Populations (8.1, 8.3) and Nonclinical Toxicology (13.1)].

6 ADVERSE REACTIONS

The following clinically significant adverse reactions are described elsewhere in the labeling:

- Cardiomyopathy [see Warnings and Precautions (5.1)]
- Secondary Malignancies [see Warnings and Precautions (5.2)]
- Severe Local Tissue Necrosis with Extravasation [see Warnings and Precautions (5.3)]
- Severe Myelosuppression [see Warnings and Precautions (5.4)]
- Tumor Lysis Syndrome [see Warnings and Precautions (5.5)]
- Hypersensitivity [see Warnings and Precautions (5.6)]

6.1 Clinical Trials and Postmarketing Experience

Because clinical trials are conducted under widely varying conditions, adverse reaction rates observed in the clinical trials of a drug cannot be directly compared to rates in the clinical trials of another drug and may not reflect the rates observed in practice.

The safety of IDAMYCIN PFS in combination with cytarabine has been evaluated in four controlled clinical studies with 823 patients with AML randomized to receive idarubicin hydrochloride (n=401) or daunorubicin (n=422) [see Clinical Studies (14)].

Southeastern Cancer Study Group (SEG)

Table 3 below lists the adverse reactions that occurred in patients with AML who received idarubicin hydrochloride in the Southeastern Cancer Study Group (SEG) study.

Table 3: Adverse Reactions (≥5%) in Patients with AML Who Received Idarubicin Hydrochloride as Induction Therapy in the SEG Trial
Adverse Reactions | Idarubicin with Cytarabine; (N=110) | Daunorubicin with Cytarabine; (N=118)
Adverse Reactions | All Grades; % | All Grades; %
Infection | 95 | 97
Nausea/Vomiting | 82 | 80
Alopecia | 77 | 72
Abdominal Pain/Diarrhea | 73 | 68
Hemorrhage | 63 | 65
Mucositis | 50 | 55
Dermatologic | 46 | 40
Mental Status Changes | 41 | 34
Pulmonary Disorders | 39 | 39
Fever | 26 | 28
Headache | 20 | 24
Cardiac Disorder | 16 | 24
Peripheral Neuropathy | 7 | 9

Clinically relevant adverse reactions in <5% of patients who received idarubicin hydrochloride included pulmonary allergy, seizure, and cerebellar adverse reactions.

Other Clinical Trials

The following additional adverse reactions associated with the use of idarubicin hydrochloride were identified in clinical studies or postmarketing reports. Because some of these reactions were reported voluntarily from a population of uncertain size, it is not always possible to reliably estimate their frequency or establish a causal relationship to drug exposure.

Cardiac

- Asymptomatic declines in Left Ventricular Ejection Fraction (LVEF)
- Chest pain
- Congestive heart failure
- Myocardial infarction
- Serious arrhythmias including atrial fibrillation

Dermatologic

- Bullous erythrodermatous rash (palms and soles)
- Generalized rash
- Radiation recall (skin reaction)
- Urticaria

Gastrointestinal

- Severe enterocolitis with perforation

Hepatic

- Increased ALT/AST

Renal

- Renal impairment

8 USE IN SPECIFIC POPULATIONS

8.1 Pregnancy

Risk Summary

Based on findings from animal reproduction studies and its mechanism of action, IDAMYCIN PFS can cause fetal harm when administered to a pregnant woman [see Warnings and Precautions (5.9)]. There are no available data on the use of IDAMYCIN PFS in pregnant women to evaluate for a drug-associated risk.

Idarubicin hydrochloride was embryotoxic and teratogenic in rats at doses of 1.2 mg/m^2/day or 0.1 times the human dose. Idarubicin hydrochloride was embryotoxic but not teratogenic in rabbits at doses of 2.4 mg/m^2/day or 0.2 times the human dose [see Data]. Advise women of the potential risk to the fetus.

In the U.S. general population, the estimated background risk of major birth defects and miscarriage in clinically recognized pregnancies is 2% to 4% and 15% to 20%, respectively.

Data

Animal Data

Idarubicin hydrochloride was embryotoxic and teratogenic in the rat at a dose of 1.2 mg/m^2/day or 0.1 times the human dose, which was not maternally toxic. Idarubicin hydrochloride was embryotoxic but not teratogenic in the rabbit even at a dose of 2.4 mg/m^2/day or 0.2 times the human dose, which was maternally toxic.

8.2 Lactation

Risk Summary

There are no data on the presence of idarubicin hydrochloride or its metabolites in human milk, the effects on the breastfed child or the effects on milk production. Because of the potential for serious adverse reactions in the breastfed child, including myelosuppression, cardiac toxicity and malignancy, advise women not to breastfeed during treatment with IDAMYCIN PFS and for 14 days after the last dose.

8.3 Females and Males of Reproductive Potential

Based on mechanism of action and findings in animals, IDAMYCIN PFS can cause fetal harm [see Use in Specific Populations (8.1)].

Pregnancy Testing

Verify the pregnancy status of female patients of reproductive potential prior to initiating therapy with IDAMYCIN PFS.

Contraception

Females

Advise females of reproductive potential to use effective contraception during treatment with IDAMYCIN PFS and for 6.5 months after the last dose.

Males

Based on the genotoxicity potential, advise males with female partners of reproductive potential to use effective contraception during treatment with IDAMYCIN PFS and for 3.5 months after the last dose.

Infertility

Based on animal studies and mechanism of action, IDAMYCIN PFS may impair fertility in males and females of reproductive potential [see Nonclinical Toxicology (13.1)]. It is not known if these effects are reversible.

8.4 Pediatric Use

The safety and effectiveness of IDAMYCIN PFS in pediatric patients have not been established. Pediatric patients may be at greater risk for anthracycline-induced acute manifestations of cardiotoxicity or late cardiovascular dysfunction.

The safety and effectiveness of idarubicin hydrochloride were assessed but not established in two open label clinical studies in pediatric patients aged 1 to <17 years with leukemia and solid tumors. The pharmacokinetics of idarubicin hydrochloride in these pediatric patients were within range of that observed in adult patients given a similar dose based on body surface area.

Idarubicin hydrochloride and idarubicinol were detected in CSF samples obtained in these patients; the clinical relevance of these findings is unknown.

8.5 Geriatric Use

Patients over 60 years of age who were undergoing induction therapy experienced congestive heart failure, serious arrhythmias, chest pain, myocardial infarction, and asymptomatic declines in LVEF more frequently than younger patients [see Adverse Reactions (6.1)].

8.6 Renal Impairment

Reduce dosage of IDAMYCIN PFS in patients with GFR less than 30 mL/min and in patients on hemodialysis [see Dosage and Administration (2.3)]. Renal function should be evaluated prior to and during treatment with IDAMYCIN PFS.

The effect of renal impairment on idarubicin hydrochloride or idarubicinol pharmacokinetics is unknown [see Clinical Pharmacology (12.3)]. However, renal impairment can affect the disposition of idarubicin hydrochloride based on a mechanistic understanding of idarubicin hydrochloride elimination. Treatment was not given if creatinine serum levels exceeded 2 mg/dL in multiple clinical trials.

8.7 Hepatic Impairment

Reduce dosage of IDAMYCIN PFS in patients with serum bilirubin levels greater than 2.6 mg/dL and less than 5 mg/dL [see Dosage and Administration (2.4)]. Do not administer IDAMYICN PFS in patients with serum bilirubin levels greater than 5 mg/dL. Liver function should be evaluated prior to and during treatment with IDAMYCIN PFS.

The effect of hepatic impairment on idarubicin hydrochloride or idarubicinol pharmacokinetics is unknown [see Clinical Pharmacology (12.3)]. However, hepatic impairment can affect the disposition of idarubicin hydrochloride based on a mechanistic understanding of idarubicin hydrochloride elimination.

10 OVERDOSAGE

There is no known antidote to idarubicin hydrochloride. Two cases of fatal overdosage in patients receiving therapy for AML have been reported. The doses were 135 mg/m^2 over 3 days and 45 mg/m^2 of idarubicin hydrochloride and 90 mg/m^2 of daunorubicin over a three-day period.

Based on multicompartment and extravascular distribution, tissue binding, and low unbound fraction available in plasma, hemodialysis or peritoneal dialysis are unlikely to significantly reduce exposure during an overdosage.

11 DESCRIPTION

IDAMYCIN PFS contains idarubicin hydrochloride, which is an anthracycline topoisomerase inhibitor.

Chemically, idarubicin hydrochloride is 5, 12-Naphthacenedione, 9-acetyl-7-[(3-amino-2,3,6-trideoxy-α-L-lyxo-hexopyranosyl)oxy]-7,8,9,10-tetrahydro-6,9,11-trihydroxyhydrochloride, (7S-cis). The structural formula is as follows:

C26 H27 NO9 ∙HCl M.W. 533.96

IDAMYCIN PFS injection, for intravenous use, is a sterile, orange-red, isotonic parenteral preservative-free solution, available in 5 mL (5 mg), 10 mL (10 mg), and 20 mL (20 mg) single-dose only vials.

Each mL contains idarubicin hydrochloride, USP 1 mg (equivalent to 0.93 mg idarubicin free base) and the following inactive ingredients: Glycerin, USP 25 mg and Water for Injection, USP q.s. Hydrochloric Acid, NF is used to adjust the pH to a target of 3.5.

12 CLINICAL PHARMACOLOGY

12.1 Mechanism of Action

Idarubicin hydrochloride has antimitotic and cytotoxic activity through forming complexes with the DNA, inhibiting nucleic acid synthesis, inhibiting topoisomerase II activity, and producing DNA-damaging free radicals.

12.2 Pharmacodynamics

Idarubicin hydrochloride exposure-response relationships and the time course of pharmacodynamic response have not been fully characterized.

12.3 Pharmacokinetics

Idarubicin hydrochloride pharmacokinetics were determined in adult leukemia patients with normal renal and hepatic function following intravenous administration of idarubicin hydrochloride 10 to 12 mg/m^2 daily for 3 to 4 days as a single agent or combined with cytarabine.

Accumulation is predicted to be 1.7-fold for idarubicin hydrochloride and 2.3-fold for idarubicinol following multiple idarubicin hydrochloride dosing.

Distribution

Idarubicin hydrochloride exhibits a rapid distributive phase with a very large volume of distribution. Idarubicin hydrochloride is approximately 97% and idarubicinol is 94% bound to plasma proteins and the binding is concentration independent.

Concentrations of idarubicin hydrochloride and idarubicinol in nucleated blood and bone marrow cells are more than a hundred times the plasma concentrations.

Elimination

Idarubicin hydrochloride mean (range) terminal half-life is 22 (4 to 48) hours when used as a single agent and 20 (7 to 38) hours when used in combination with cytarabine. Idarubicin hydrochloride plasma clearance is twice the expected hepatic plasma flow.

Idarubicinol mean terminal half-life exceeds 45 hours; hence, its plasma levels are sustained for a period greater than 8 days.

Metabolism

The idarubicin hydrochloride is primary metabolized to the active metabolite idarubicinol which has cytotoxic activity that likely contributes to the effects of idarubicin hydrochloride.

Excretion

Idarubicin hydrochloride is eliminated predominately by biliary excretion and to a lesser extent by renal excretion, primarily as idarubicinol.

Specific Populations

The effect of renal or hepatic impairment on idarubicin hydrochloride or idarubicinol pharmacokinetics is unknown.

13 NONCLINICAL TOXICOLOGY

13.1 Carcinogenesis, Mutagenesis, Impairment of Fertility

Carcinogenicity studies have not been conducted with idarubicin hydrochloride. Idarubicin hydrochloride and related compounds have been shown to have mutagenic and carcinogenic properties when tested in experimental models (including bacterial systems, mammalian cells in culture and female Sprague Dawley rats).

In male dogs given 1.8 mg/m^2/day 3 times/week (about one seventh the weekly human dose on a mg/m^2 basis) for 13 weeks, or 3 times the human dose, testicular atrophy was observed with inhibition of spermatogenesis and sperm maturation with few or no mature sperm. These effects were not readily reversed after a recovery of 8 weeks.

14 CLINICAL STUDIES

The efficacy of IDAMYCIN PFS was evaluated in four randomized, controlled clinical studies (Memorial Sloan Kettering Cancer Center (MSKCC), Southeastern Cancer Study Group (SEG), US Multicenter, and Gruppo Italiano Malattie Ematologiche Maligne dell’Adulto (GIMEMA) trials) of 823 adult patients with newly-diagnosed AML. Patients were randomized to receive either idarubicin hydrochloride (IDR) or daunorubicin (DNR) in combination with cytarabine (Ara C) as induction therapy. Median age for IDR versus DNR in the MSKCC, SEG, US Multicenter, and GIMEMA studies was 36 versus 41, 60 versus 61, 56 versus 55, and 63 versus 62 years, respectively. Incidence of male sex was 45% versus 46%, 53% versus 47%, 57% versus 56%, and 52% versus 59%, respectively.

Idarubicin hydrochloride was administered as an induction regimen of 12 mg/m^2 (or 13 mg/m^2 [1.1 times the recommended dosage] in US Multicenter study only) once a day for 3 days in combination with cytarabine. Daunorubicin was administered as an induction regimen of 45 mg/m^2 (or 50 mg/m^2 in MSKCC study only) daily for 2 days. Cytarabine was administered 100 mg/m^2 daily by continuous infusion for 7 days or as 25 mg/m^2 intravenous bolus followed by 200 mg/m^2 daily for 5 days continuous infusion (MSKCC only). Patients who had persistent leukemia after the first induction course could receive a second course of induction therapy.

Patients received the same anthracycline for consolidation as was used for induction, in combination with cytarabine (and 6-thioguanine for the SEG study only). The SEG study also included maintenance therapy with the same anthracycline used in induction in combination with cytarabine. The efficacy or safety have not been established for IDAMYCIN PFS for use as consolidation or maintenance therapy. Efficacy results for the four trials are provided in Table 4.

Table 4: Efficacy Results in Patients with AML in MSKCC, SEG, US Multicenter, and GIMEMA Studies [All randomized patients]
 | MSKCC |  | SEG |  | US Multicenter |  | GIMEMA
 | IDR + Ara C | DNR + Ara C | IDR + Ara C | DNR + Ara C | IDR + Ara C | DNR + Ara C | IDR + Ara C | DNR + Ara C
Complete Remission Rate n/N (%) | 51/65 [Overall p <0.05, unadjusted for prognostic factors or multiple endpoints]; (78%) | 38/65; (58%) | 76/111; (68%) | 65/119; (55%) | 68/101; (67%) | 66/113; (58%) | 49/124; (40%) | 49/125; (39%)
Median Overall Survival (months) | 16.7 | 14.3 | 10.8 | 9.1 | 12.9 | 9.2 | 2.9 | 5.6

15 REFERENCES

1. "OSHA Hazardous Drugs." OSHA. http://www.osha.gov/SLTC/hazardousdrugs/index.html.

16 HOW SUPPLIED/STORAGE AND HANDLING

How Supplied

IDAMYCIN PFS (idarubicin hydrochloride) injection is a clear, orange-red, aqueous, preservative-free solution available as follows:

Single-dose Cytosafe™ vials:

Unit of Sale | Concentration
NDC 0013-2576-91; Carton of 1 Single-dose Vial | 5 mg/5 mL; (1 mg/mL)
NDC 0013-2586-91; Carton of 1 Single-dose Vial | 10 mg/10 mL; (1 mg/mL)
NDC 0013-2596-91; Carton of 1 Single-dose Vial | 20 mg/20 mL; (1 mg/mL)

Single-dose glass vials:

Unit of Sale | Concentration
NDC 0013-2576-05; Carton of 1 Single-dose Vial | 5 mg/5 mL; (1 mg/mL)
NDC 0013-2586-10; Carton of 1 Single-dose Vial | 10 mg/10 mL; (1 mg/mL)
NDC 0013-2596-20; Carton of 1 Single-dose Vial | 20 mg/20 mL; (1 mg/mL)

Storage and Handling

Store refrigerated at 2ºC to 8ºC (36ºF to 46ºF). Store and dispense in the original carton until time of use to protect from light.

IDAMYCIN PFS is a hazardous drug. Follow applicable special handling and disposal procedures.^1

17 PATIENT COUNSELING INFORMATION

Cardiomyopathy

Inform patients that IDAMYCIN PFS can cause irreversible myocardial damage. Advise patients to immediately contact their healthcare provider during or after treatment with IDAMYCIN PFS for symptoms of heart failure, including new onset or worsening shortness of breath, cough, swelling of the ankles/legs, swelling of the face, palpitations, weight gain of more than 5 pounds in 24 hours, dizziness, or loss of consciousness [see Warnings and Precautions (5.1)].

Secondary Malignancies

Inform patients that there is an increased risk of secondary malignancies with IDAMYCIN PFS [see Warnings and Precautions (5.2)].

Extravasation and Tissue Necrosis

Inform patients that IDAMYCIN PFS can cause severe injection site reactions. Advise patients to contact a healthcare provider if injection site pain occurs after receiving IDAMYCIN PFS [see Warnings and Precautions (5.3)].

Severe Myelosuppression

Inform patients that IDAMYCIN PFS causes bone marrow suppression at therapeutic doses resulting in an increased risk of infection or hemorrhage. Advise patients to contact their healthcare provider for new onset fever or symptoms of infection or hemorrhage [see Warnings and Precautions (5.4)].

Tumor Lysis Syndrome

Advise patients to contact their healthcare provider promptly to report any signs and symptoms of tumor lysis syndrome (fever, chills, nausea, vomiting, confusion, shortness of breath, seizure, irregular heartbeat, dark or cloudy urine, unusual tiredness, muscle pain, and/or joint discomfort) [see Warnings and Precautions (5.5)].

Alopecia

Inform patients that IDAMYCIN PFS causes alopecia (usually reversible) in most patients [see Adverse Reactions (6.1)].

Red Discoloration of Bodily Fluids

Inform patients that IDAMYCIN PFS may transiently impart a red coloration to bodily fluids, including the urine, after administration.

Gastrointestinal Adverse Reactions

Inform patients that IDAMYCIN PFS can cause nausea, vomiting, diarrhea, and mucositis. Advise patients to contact a healthcare provider if nausea, vomiting, diarrhea, or mucositis occur [see Adverse Reactions (6.1)].

Embryo-Fetal Toxicity

IDAMYCIN PFS can cause fetal harm. Advise females of reproductive potential to inform their healthcare provider of a known or suspected pregnancy [see Warnings and Precautions (5.9), Use in Specific Populations (8.1, 8.3), and Nonclinical Toxicology (13.1)].

Advise female patients of reproductive potential to use effective contraception during treatment with IDAMYCIN PFS and for 6.5 months after the last dose [see Warnings and Precautions (5.9), Use in Specific Populations (8.1, 8.3), and Nonclinical Toxicology (13.1)].

Advise male patients with female partners of reproductive potential to use effective contraception during treatment and for 3.5 months after the last dose of IDAMYCIN PFS. [see Warnings and Precautions (5.9), Use in Specific Populations (8.1, 8.3), and Nonclinical Toxicology (13.1)].

Lactation

Advise women not to breastfeed during treatment with IDAMYCIN PFS and for 14 days after the last dose [see Use in Specific Populations (8.2)].

Infertility

Advise male and female patients of reproductive potential that IDAMYCIN PFS may impair fertility [see Use in Specific Populations (8.3) and Nonclinical Toxicology (13.1)].

This product’s labeling may have been updated. For the most recent prescribing information, please visit www.pfizer.com.

LAB-0131-10.0

PRINCIPAL DISPLAY PANEL - 5 mg/5 mL Vial Label

NDC 0013-2576-91

5 mL Single-Dose CYTOSAFE® Vial

Idamycin PFS®
idarubicin hydrochloride
injection

5 mg/5 mL
(1 mg/mL)

For IV use only
Sterile, Isotonic Solution

Rx only

PRINCIPAL DISPLAY PANEL - 5 mL Vial Carton

NDC 0013-2576-91

5 mL Single-Dose CYTOSAFE® Vial

Idamycin PFS®
idarubicin hydrochloride
injection

5 mg/5 mL
(1 mg/mL)

For IV use only
Sterile, Isotonic Solution

Pfizer
Hospital

Rx only

PRINCIPAL DISPLAY PANEL - 5 mg/5 mL Glass Vial Label

NDC 0013-2576-05

5 mL Single-Dose Vial

Idamycin PFS®
idarubicin hydrochloride injection

5 mg/5 mL
(1 mg/1 mL)
For Intravenous Use Only
Caution: Cytotoxic Agent
Sterile: Isotonic Solution

Rx only

PRINCIPAL DISPLAY PANEL - 5 mg/5 mL Glass Vial Carton

NDC 0013-2576-05

5 mL Single-Dose Vial
Discard unused portion

Idamycin PFS®
idarubicin hydrochloride
injection

5 mg/5 mL
(1 mg/mL)

For Intravenous Use Only
Sterile, Isotonic Solution

Pfizer
Hospital

Rx only

PRINCIPAL DISPLAY PANEL - 10 mg/10 mL Vial Label

NDC 0013-2586-91

10 mL Single-Dose CYTOSAFE® Vial

Idamycin PFS®
idarubicin hydrochloride
injection

10 mg/10 mL
(1 mg/mL)

For IV use only
Sterile, Isotonic Solution

Rx only

PRINCIPAL DISPLAY PANEL - 10 mL Vial Carton

NDC 0013-2586-91

10 mL Single-Dose CYTOSAFE® Vial

Idamycin PFS®
idarubicin hydrochloride
injection

10 mg/10 mL
(1 mg/mL)

For IV use only
Sterile, Isotonic Solution

Pfizer
Hospital

Rx only

PRINCIPAL DISPLAY PANEL - 10 mg/10 mL Glass Vial Label

10 mL Single- Dose Vial
NDC 0013-2586-10

Idamycin PFS®
idarubicin hydrochloride injection

10 mg/10 mL
(1 mg/mL)
For Intravenous Use Only
Caution: Cytotoxic Agent
Sterile, Isotonic Solution
GUJ-DRUGS/G/28/1267
Rx only

PRINCIPAL DISPLAY PANEL - 10 mg/10 mL Glass Vial Carton

NDC 0013-2586-10

10 mL Single-Dose Vial

Discard unused portion

Idamycin PFS®
idarubicin hydrochloride
injection

10 mg/10 mL
(1 mg/mL)

For Intravenous Use Only
Sterile, Isotonic Solution

Pfizer
Hospital

Rx only

PRINCIPAL DISPLAY PANEL - 20 mg/20 mL Vial Label

NDC 0013-2596-91

20 mL Single-Dose CYTOSAFE® Vial

Idamycin PFS®
idarubicin hydrochloride
injection

20 mg/20 mL
(1 mg/mL)

For IV use only
Sterile, Isotonic Solution

PRINCIPAL DISPLAY PANEL - 20 mL Vial Carton

NDC 0013-2596-91

20 mL Single-Dose CYTOSAFE® Vial

Idamycin PFS®
idarubicin hydrochloride
injection

20 mg/20 mL
(1 mg/mL)

For IV use only
Sterile, Isotonic Solution

Pfizer
Hospital

Rx only

PRINCIPAL DISPLAY PANEL - 20 mg/20 mL Glass Vial Label

NDC 0013-2596-20

20 mL Single-Dose Vial

Idamycin PFS®
idarubicin hydrochloride
injection

20 mg/20 mL
(1 mg/mL)

For Intravenous Use Only
Caution: Cytotoxic Agent
Sterile, Isotonic Solution

Rx only

PRINCIPAL DISPLAY PANEL - 20 mg/20 mL Glass Vial Carton

NDC 0013-2596-20

20 mL Single-Dose Vial
Discard unused portion

Idamycin PFS®
idarubicin hydrochloride
injection

20 mg/20 mL
(1 mg/mL)

For Intravenous Use Only
Sterile, Isotonic Solution

Pfizer
Hospital

Rx only